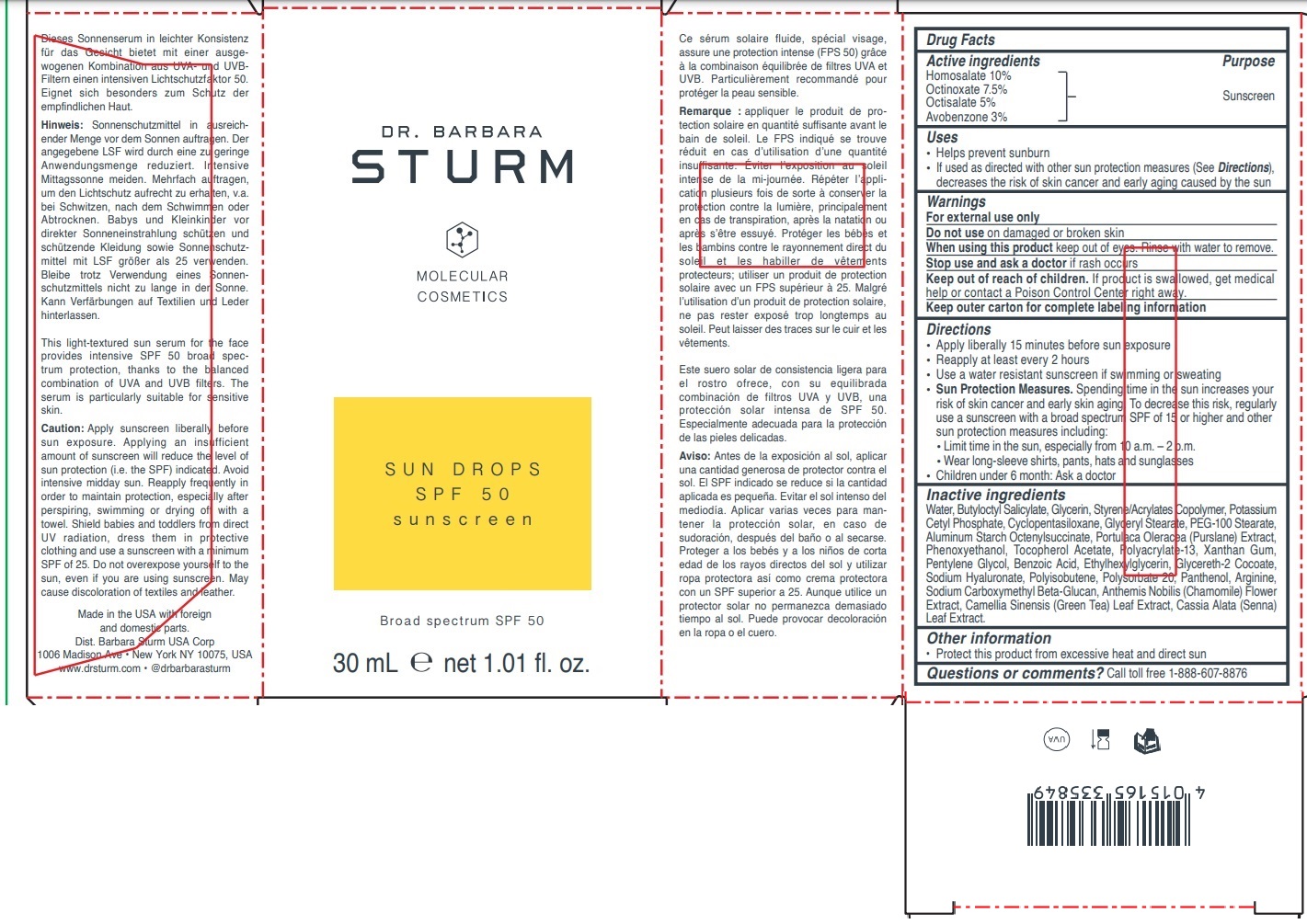 DRUG LABEL: DR. BARBARA STURM MOLECULAR COSMETICS SPF 50 sunscreen
NDC: 83175-232 | Form: LIQUID
Manufacturer: Barbara Sturm Molecular Cosmetics GmbH
Category: otc | Type: HUMAN OTC DRUG LABEL
Date: 20241217

ACTIVE INGREDIENTS: HOMOSALATE 10 g/100 mL; OCTINOXATE 7.5 g/100 mL; OCTISALATE 5 g/100 mL; AVOBENZONE 3 g/100 mL
INACTIVE INGREDIENTS: WATER; BUTYLOCTYL SALICYLATE; GLYCERIN; STYRENE/ACRYLAMIDE COPOLYMER (500000 MW); POTASSIUM CETYL PHOSPHATE; CYCLOMETHICONE 5; GLYCERYL MONOSTEARATE; PEG-100 MONOSTEARATE; ALUMINUM STARCH OCTENYLSUCCINATE; PURSLANE; PHENOXYETHANOL; .ALPHA.-TOCOPHEROL ACETATE; POLYACRYLATE-13; XANTHAN GUM; PENTYLENE GLYCOL; BENZOIC ACID; ETHYLHEXYLGLYCERIN; GLYCERETH-2 COCOATE; HYALURONATE SODIUM; POLYISOBUTYLENE (1000 MW); POLYSORBATE 20; PANTHENOL; ARGININE; SODIUM CARBOXYMETHYL .BETA.-GLUCAN (DS 0.65-0.85); CHAMAEMELUM NOBILE FLOWER; GREEN TEA LEAF; SENNA ALATA LEAF

DR. BARBARA STURM MOLECULAR COSMETICS SPF 50 sunscreen

Active ingredients

Homosalate 10%
Octinoxate 7.5%
Octisalate 5%
Avobenzone 3%

Purpose

Sunscreen

Uses

• Helps prevent sunburn
• If used as directed with other sun protection measures (see Directions), decreases the risk of skin cancer and early skin aging caused by the sun

Warnings

For external use only

Do not use on damaged or broken skin

When using this product keep out of eyes. Rinse with water to remove.

Stop use and ask a doctor if rash occurs

Keep out of reach of children. If product is swallowed, get medical help or contact a Poison Control Center right away.

Keep outer carton for complete labeling information

Directions

• Apply liberally 15 minutes before sun exposure
• Reapply at least every 2 hours
• Use a water resistant sunscreen if swimming or sweating
• Sun Protection Measures. Spending time in the sun increases your risk of skin cancer and early skin aging. To decrease this risk, regularly use a sunscreen with a broad spectrum SPF of 15 or higher and other sun protection measures including:
• Limit time in the sun, especially from 10 a.m. - 2 p.m.
• Wear long-sleeve shirts, pants, hats and sunglasses
• Children under 6 months: Ask a doctor

Inactive ingredients

Water, Butyloctyl Salicylate, Glycerin, Styrene/Acrylates Copolymer, Potassium Cetyl Phosphate, Cyclopentasiloxane, Glyceryl Stearate, PEG-100 Stearate, Aluminum Starch Octenylsuccinate, Portulaca Oleracea (Purslane) Extract, Phenoxyethanol, Tocopherol Acetate, Polyacrylate-13, Xanthan Gum, Pentylene Glycol, Benzoic Acid, Ethylhexylglycerin, Glycereth-2 Cocoate, Sodium Hyaluronate, Polyisobutene, Polysorbate 20, Panthenol, Arginine, Sodium Carboxymethyl Beta-Glucan, Anthemis Nobilis (Chamomile) Flower Extract, Camellia Sinensis (Green Tea) Leaf Extract, Cassia Alata (Senna) Leaf Extract.

Other information

• Protect this product from excessive heat and direct sun

Questions or comments?

Call toll free 1-888-607-8876

SUN DROPS

Broad Spectrum SPF 50

This light-textured sun serum for the face provides intensive SPF 50 broad spectrum protection, thanks to the balanced combination of UVA and UVB filters. The serum is particularly suitable for sensitive skin.

Caution: Apply sunscreen liberally before sun exposure. Applying an insufficient amount of sunscreen will reduce the level of sun protection (i.e. the SPF) indicated. Avoid intensive midday sun. Reapply frequently in order to maintain protection, especially after perspiring, swimming or drying off with a towel. Shield babies and toddlers from direct UV radiation, dress them in protective clothing and use a sunscreen with a minimum SPF of 25. Do not overexpose yourself to the sun, even if you are using sunscreen. May cause discoloration of textiles and leather.

Made in the USA with foreign and domestic parts.
Dist. Barbara Sturm USA Corp
1006 Madison Ave • New York NY 10075, USA
www.drsturm.com • @drbarbarasturm